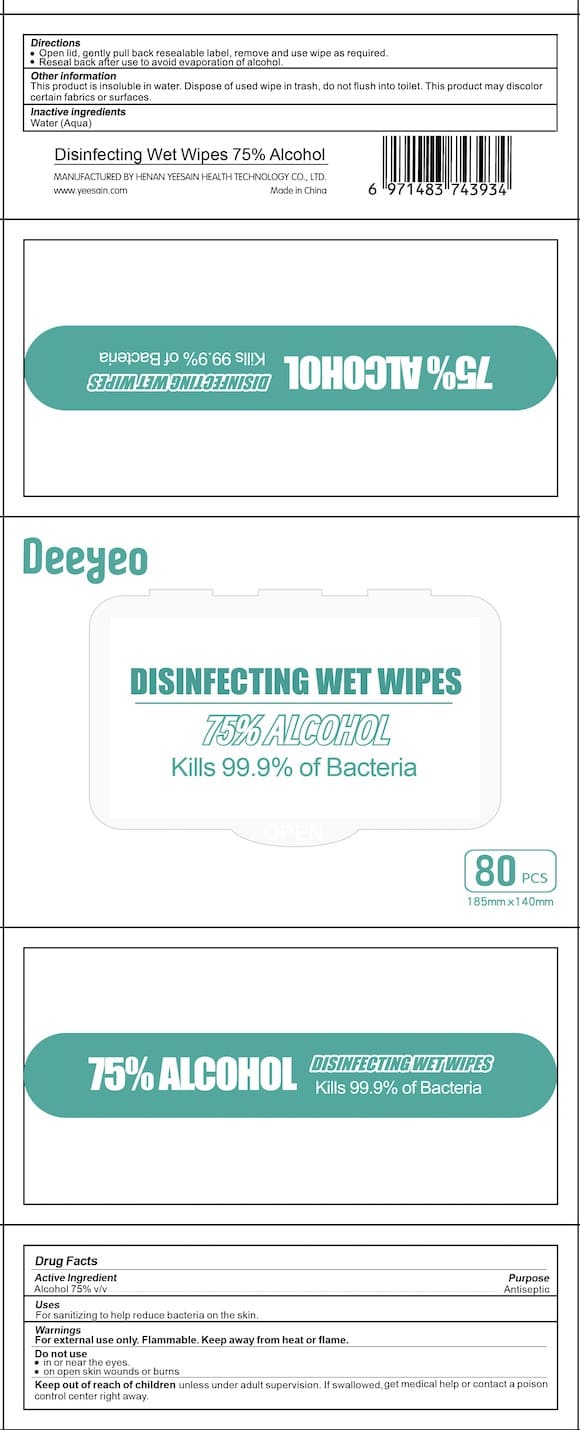 DRUG LABEL: Deeyeo
NDC: 75622-677 | Form: CLOTH
Manufacturer: Henan Yeesain Health Technology Co., Ltd.
Category: otc | Type: HUMAN OTC DRUG LABEL
Date: 20251211

ACTIVE INGREDIENTS: ALCOHOL 0.75 mL/1 1
INACTIVE INGREDIENTS: WATER

Henan Yeesain Deeyeo Alcohol Wipes

Active Ingredient(s)

Alcohol 75% v/v. Purpose: Antiseptic

Purpose

Antiseptic

Use

For sanitizing to help in reducing bacteria on the skin.

Warnings

For external use only. Flammable. Keep away from heat or flame

Do not use

- in or near the eyes.
- on open skin wounds or burns

Keep out of reach of children unless under adult supervision. If swallowed, get medical help or contact a poison control center right away

Directions

- Open lid, gently pull back resealable label, remove, and use the wipe as required.
- Reseal back after use to avoid evaporation of alcohol.

Other information

This product is insoluble in water. Dispose of used wipe in trash, do not flush into toilet. This product may discolor certain fabrics or surfaces.

Inactive ingredients

Purified Water